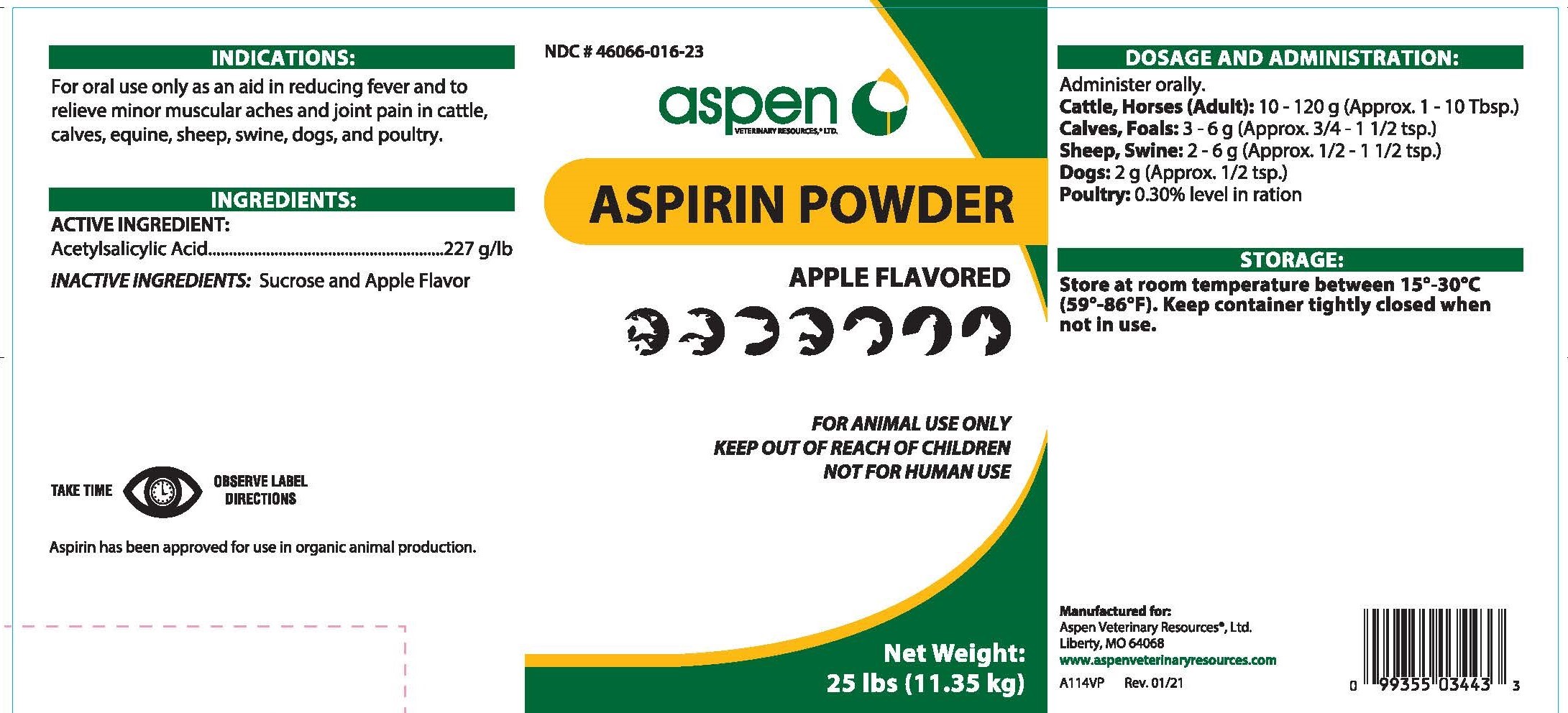 DRUG LABEL: Aspirin Powder
NDC: 46066-016 | Form: POWDER
Manufacturer: Aspen Veterinary Resources, LTD
Category: animal | Type: OTC ANIMAL DRUG LABEL
Date: 20250113

ACTIVE INGREDIENTS: ASPIRIN 500 mg/1 g

Indications:

For oral use only as an aid in reducing fever and to relieve minor muscular aches and joint pain in cattle, calves, equine, sheep, swine, dogs, and poultry.

Ingredients: Active Ingredient:

Acetylsalicylic Acid ............227g/lb

Ingredients: Inactive Ingredients:

Sucrose and Apple Flavor

Dosage and Administration

Administer Orally.

Cattle, Horses (Adult): 10-120g (approx. 1-10 Tbsp.)

Calves, Foals: 3-6g (approx. 3/4-1 1/2 tsp.)

Sheep, Swine: 2-6g (approx. 1/2-1 1/2 tsp.)

Dogs: 2g (approx. 1/2 tsp.)

Poultry: 0.30% level in ration

Storage:

Store at room temperature between 15°C-30°C (59-86°F). Keep container tightly closed when not in use.

PACKAGE LABEL

Add image transcription here...

Add image transcription here...